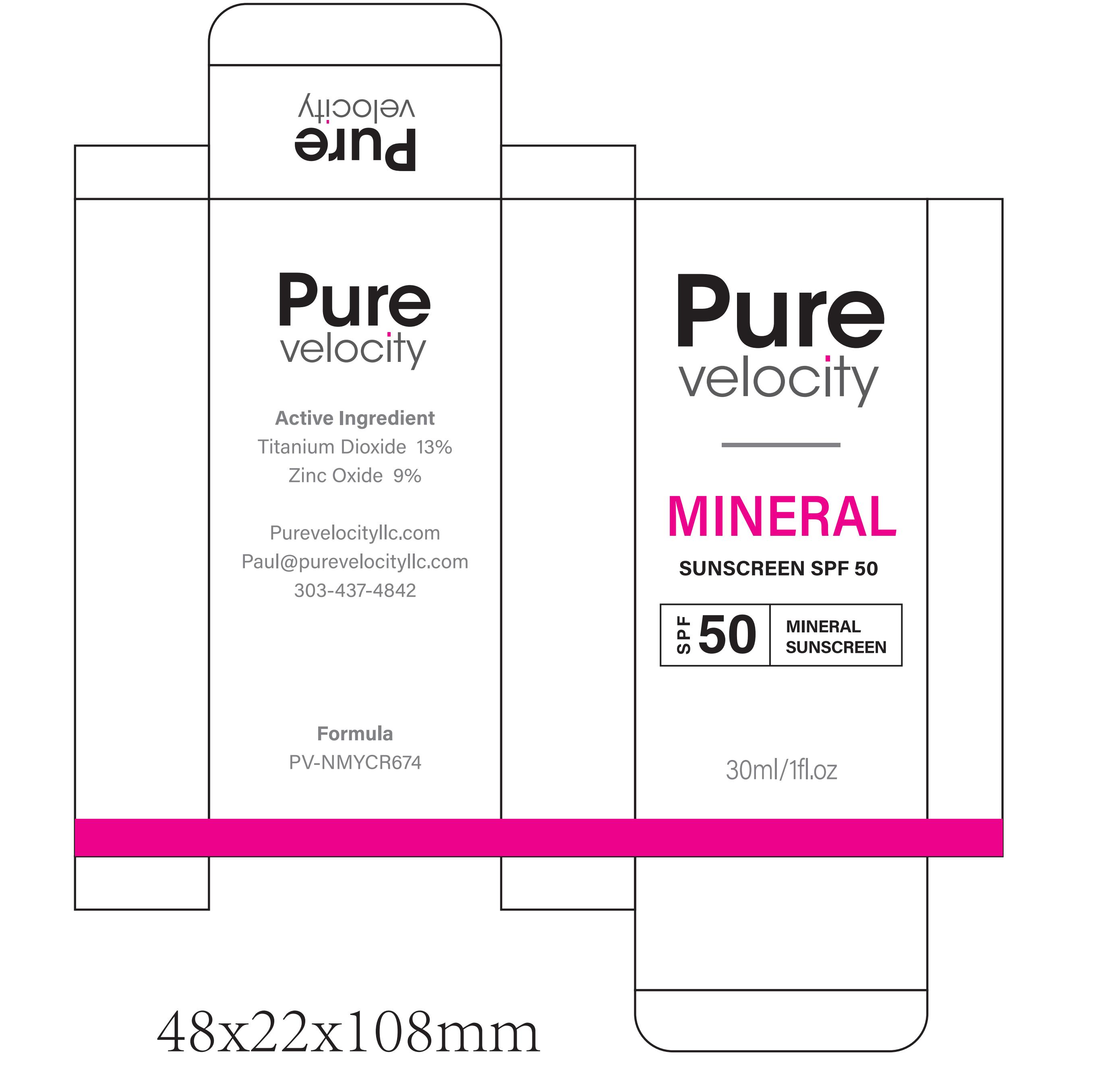 DRUG LABEL: Pure velocity MINERAL SUNSCREEN SPF 50
NDC: 60771-0032 | Form: CREAM
Manufacturer: Guangzhou Haishi Biological Technology Co., Ltd.
Category: otc | Type: HUMAN OTC DRUG LABEL
Date: 20250930

ACTIVE INGREDIENTS: TITANIUM DIOXIDE 3.9 g/100 mL; ZINC OXIDE 2.7 g/100 mL
INACTIVE INGREDIENTS: TRITICUM VULGARE (WHEAT) GERM; CETEARYL ALCOHOL; CHLORPHENESIN; TRITICUM VULGARE (WHEAT) GERM OIL; WATER; SODIUM HYALURONATE; C12-15 ALKYL BENZOATE; CETEARYL GLUCOSIDE; BISABOLOL; PAEONIA ALBIFLORA FLOWER; ETHYLHEXYLGLYCERIN; ALOE FEROX LEAF JUICE; CENTELLA ASIATICA ROOT; NIACINAMIDE; PARFUMIDINE; 1,3-BETA-GLUCAN SYNTHASE COMPONENT FKS1; DIMETHICONE; DIPROPYLENE GLYCOL; TREHALOSE; ALLANTOIN; ETHYLHEXYL SALICYLATE; ASCORBIC ACID; CETEARETH-22; LIMNANTHES ALBA (MEADOWFOAM) SEED OIL; TOCOPHEROL; XANTHAN GUM; GLYCERIN; DIPOTASSIUM GLYCYRRHIZATE; MACADAMIA TERNIFOLIA SEED OIL

Active Ingredients

TITANIUM DIOXIDE

ZINC OXIDE

Purpose

SUNSCREEN

Uses

If used as directed with other sun protection measures(see Directions)，
decreases the risk of skin cancer and early skin aging caused by the sun.

Warnings

For external use only

Stop Use

Rinse with wate to remove.
Stop use and ask doctor if rash occurs.

Do not use on damaged or broken skin.

When Using

When using this product keep out of eyes.

Keep Out Of Reach Of Children

Inactive ingredients

WATER
ASCORBIC ACID
TITANIUM DIOXIDE
ZINC OXIDE
NIACINAMIDE
PROPYLENE GLYCOL
GLYCERIN
TREHALOSE
ALLANTOIN
SODIUM HYALURONATE
DIPOTASSIUM GLYCYRRHIZATE
LIMNANTHES ALBA (MEADOWFOAM) SEED OIL
MACADAMIA TERNIFOLIA SEED OIL
TRITICUM VULGARE (WHEAT) GERM OIL
ETHYLHEXYL SALICYLATE
C12-15 ALKYL BENZOATE
CETEARYL ALCOHOL
CETEARYL GLUCOSIDE
CETEARETH-21
DIMETHICONE
TOCOPHERYL ACETATE
BISABOLOL
XANTHAN GUM
ETHYLHEXYLGLYCERIN
CHLORPHENESIN
HYDROLYZED BETA-GLUCAN
PAEONIA ALBIFLORA ROOT EXTRACT
TRITICUM VULGARE (WHEAT) GERM EXTRACT
CENTELLA ASIATICA ROOT EXTRACT
ALOE FEROX LEAF EXTRACT
PARFUM

Dosage & administration

Squeeze out an appropriate amount of Sunscreen and spread evenly on skin.